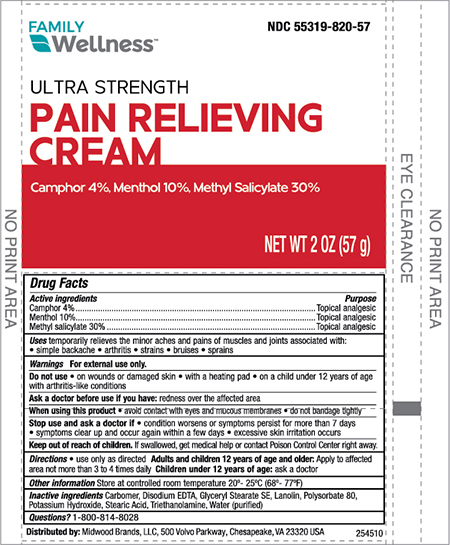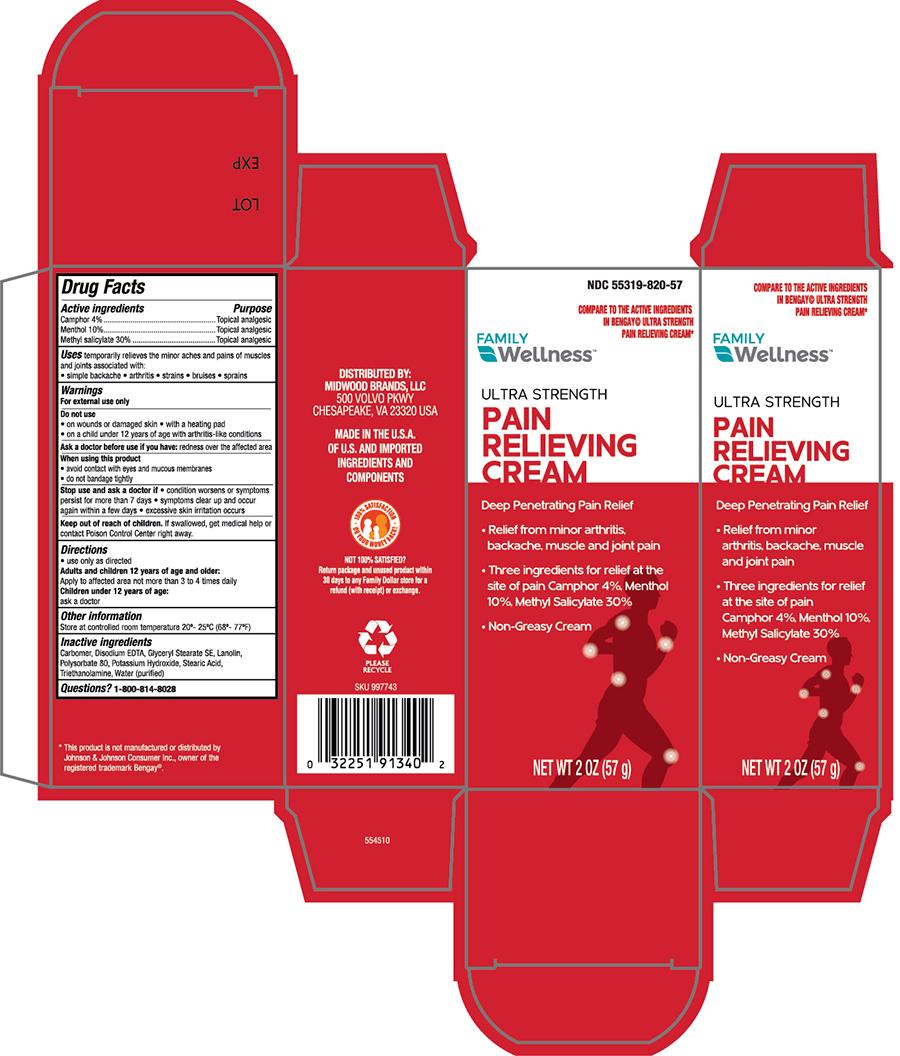 DRUG LABEL: Family Wellness Ultra Strength Muscle Rub
NDC: 55319-820 | Form: CREAM
Manufacturer: FAMILY DOLLAR (Family Wellness)
Category: otc | Type: HUMAN OTC DRUG LABEL
Date: 20241121

ACTIVE INGREDIENTS: CAMPHOR (SYNTHETIC) 40 mg/1 g; MENTHOL, UNSPECIFIED FORM 100 mg/1 g; METHYL SALICYLATE 300 mg/1 g
INACTIVE INGREDIENTS: CARBOMER 940; EDETATE DISODIUM ANHYDROUS; GLYCERYL STEARATE SE; LANOLIN; POLYSORBATE 80; POTASSIUM HYDROXIDE; STEARIC ACID; TROLAMINE; WATER

Family Wellness Ultra Strength Muscle Rub Cream

Active Ingredients

Camphor- 4%

Menthol - 10%

Methyl salicylate -30%

Purpose

Topical Analgesic

Topical Analgesic

Topical Analgesic

Uses

For temporary relief of minor aches and pains of muscle and joints associated with;

- simple backaches, arthritis, strains, bruises and sprains

Warnings

For external use only

Do not use

- on wounds or damaged skin
- with a heating pad
- on a child under 12 years of age with arthritis-like condiitions

Ask a doctor before use if you have; redness over thre affected area

When using this product

- avoid contact with eyes and mucous membranes
- do not bandage tightly

Stop use and ask a doctor if;

- condition worsens or symptoms persist for more than 7 days
- symptoms clear up and occur again within a few days
- excessive skin irritation occur

KEEP OUT OF REACH OF CHILDREN

Keep this and all drugs out of the reach of children. If swallowed, get medical help or contact a Poison Control Center immediately.

Directions

- Use only as directed

Adults and children 2 years of age and older;

- Apply to affected area not more than 3 to 4 times daily.

Children under 2 years of age; ask a doctor.

Other information

- Store at controlled room temperature 20°- 25°C (68° to 77°F)
- Close cap tightly afteruse.

Inactive ingredients

Carbomer, Disodium ETDA, Glyceryl Sterate SE, Lanolin, Polysorbate 80, Potassium Hydroxide, Stearic Acid, Triethanolamine, Water (purified)

Principal Display Panel -Tube

Family Wellness 55319-820-57

Ultra Strength

Pain Relief Cream

Camphor 4%, Menthol 10%, Methyl Salicylate 30%

NET WT 2.0 OZ (57g)

Principal Display Panel - Carton

Family Wellness 55319-820-57
Ultra Strength

Pain Relief Cream

Camphor 4%, Menthol 10%, Methyl Salicylate 30%

NET WT 2.0 OZ (57g)